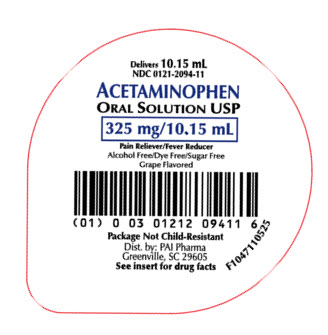 DRUG LABEL: Acetaminophen
NDC: 0121-2094 | Form: SOLUTION
Manufacturer: PAI Holdings, LLC dba PAI Pharma
Category: otc | Type: HUMAN OTC DRUG LABEL
Date: 20251211

ACTIVE INGREDIENTS: ACETAMINOPHEN 325 mg/10.15 mL
INACTIVE INGREDIENTS: ANHYDROUS CITRIC ACID; EDETATE DISODIUM; GLYCERIN; POLYETHYLENE GLYCOL 400; WATER; SODIUM BENZOATE; SODIUM METABISULFITE; SORBITOL; SUCRALOSE; SODIUM CITRATE

Acetaminophen Oral Solution USP
Alcohol Free/Dye Free/Sugar Free
Grape Flavored

Active ingredient (in each 10.15 mL)

Acetaminophen 325 mg

Purposes

Pain reliever/fever reducer

Uses

• for the temporary relief of minor aches and pains due to

- headache
- muscular aches
- backache
- sore throat
- flu
- the common cold
- toothache
- premenstrual and menstrual cramps

• for the minor pain from arthritis
• and to reduce fever

Warnings

Liver warning: This product contains acetaminophen. Severe liver damage may occur if

- adult takes more than 6 doses in 24 hours, which is the maximum daily amount
- child takes more than 5 doses in 24 hours
- taken with other drugs containing acetaminophen
- adult has 3 or more alcoholic drinks every day while using this product

Allergy alert: Acetaminophen may cause severe skin reactions. Symptoms may include:

- skin reddening
- blisters
- rash

If a skin reaction occurs, stop use and seek medical help right away.

Sore throat warning: If sore throat is severe, persists for more than 2 days, is accompanied or followed by fever, headache, rash, nausea, or vomiting, consult a doctor promptly.

Do not use

- with any other drug containing acetaminophen (prescription or nonprescription). If you are not sure whether a drug contains acetaminophen, ask a doctor or pharmacist
- if you are allergic to aetaminophen or any of the inactive ingredients of this product

Ask a doctor before use if the user
• has liver disease
• is a child with pain of arthritis

Ask a doctor or pharmacist before use if the user is taking the blood thinning drug warfarin

Stop use and ask a doctor if

- adult's pain gets worse or lasts more than 10 days
- child's pain gets worse or lasts more than 5 days
- fever gets worse or lasts more than 3 days
- redness or swelling is present
- any new symptoms appear

PREGNANCY OR BREAST FEEDING

If pregnant or breast-feeding, ask a health professional before use.

OVERDOSAGE

Overdose warning: Taking more than the recommended dose (overdose) may cause liver damage. In case of overdose, get medical help or contact a Poison Control Center right away. (1-800-222-1222). Quick medical attention is critical for adults as well as children even if you do not notice any signs or symptoms.

Directions

- do not take more than directed (see overdose warning)
- dose product from the single dose cup the product is packaged in
- mL=milliliter

age | dose
adults and children 12 years of age and over | 20.3 mL (650 mg) every 4 to 6 hours not to exceed 6 doses in a 24-hour period
children 6 to under 12 years of age | 10.15 mL (325 mg) every 4 hours not to exceed 5 doses in a 24-hour period
children under 6 years of age | consult a doctor

Other information

■ Each 10.15 mL contains: sodium 12 mg

■ store at 20° to 25°C (68° to 77°F)

INACTIVE INGREDIENT

Inactive ingredients anhydrous citric acid, edetate disodium, flavor, glycerin, polyethylene glycol 400, purified water, sodium benzoate, sodium metabisulfite, sorbitol, sucralose, trisodium citrate dihydrate

Questions or comments?

Call 1-800-845-8210. You may also report serious side effects to this phone number.

Distributed by:

PAI Pharma
Greenville,SC 29605
www.paipharma.com
R05/25

PRINCIPAL DISPLAY PANEL - 10.15 mL Cup

Delivers 10.15 mL

NDC 0121-2094-11

Acetaminophen
Oral Solution USP
325 mg/10.15 mL

Pain Reliever/Fever Reducer

Alcohol Free/Dye Free/Sugar Free
Grape Flavored

Package Not Child-Resistant

Dist. by: PAI Pharma
GREENVILLE, SC 29605
See insert for drug facts